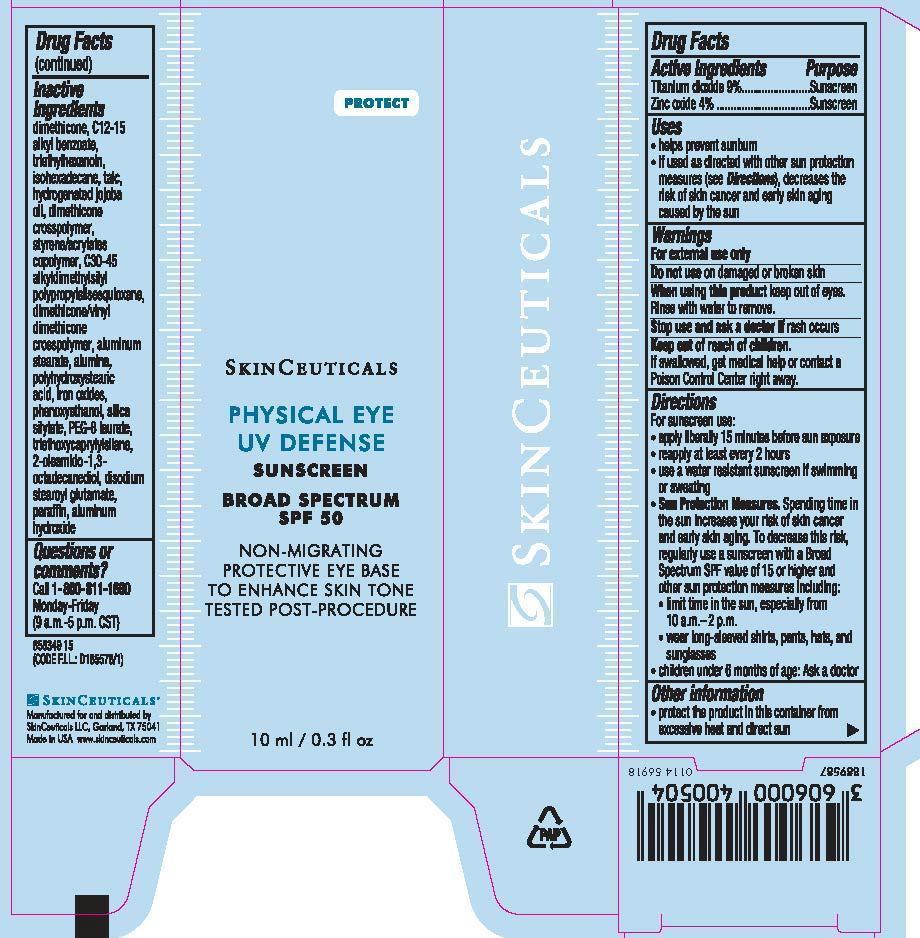 DRUG LABEL: SkinCeuticals Physical Eye UV Defense Sunscreen
NDC: 49967-050 | Form: LOTION
Manufacturer: L'Oreal USA Products Inc
Category: otc | Type: HUMAN OTC DRUG LABEL
Date: 20241228

ACTIVE INGREDIENTS: TITANIUM DIOXIDE 90 mg/1 mL; ZINC OXIDE 40 mg/1 mL
INACTIVE INGREDIENTS: DIMETHICONE; ALKYL (C12-15) BENZOATE; TRIETHYLHEXANOIN; ISOHEXADECANE; TALC; HYDROGENATED JOJOBA OIL; DIMETHICONE CROSSPOLYMER (450000 MPA.S AT 12% IN CYCLOPENTASILOXANE); STYRENE/ACRYLAMIDE COPOLYMER (500000 MW); ALUMINUM OXIDE; POLYHYDROXYSTEARIC ACID (2300 MW); FERRIC OXIDE RED; PHENOXYETHANOL; PEG-8 LAURATE; TRIETHOXYCAPRYLYLSILANE; 9-OCTADECENAMIDE, N-(2-HYDROXY-1-(HYDROXYMETHYL)HEPTADECYL)-, (9Z)-; DISODIUM STEAROYL GLUTAMATE; PARAFFIN; ALUMINUM HYDROXIDE

Drug Facts

Active ingredients

Titanium dioxide 9%

Zinc oxide 4%

Purpose

Sunscreen

Uses

- helps prevent sunburn

- if used as directed with other sun protection measures (see Directions), decreases the risk of skin cancer and early skin aging caused by the sun

Warnings

For external use only

Do not use

on damaged or broken skin

When using this product

keep out of eyes. Rinse with water to remove.

Stop use and ask a doctor if

rash occurs

Keep out of reach of children.

If swallowed, get medical help or contact a Poison Control Center right away.

Directions

For sunscreen use:

● apply liberally 15 minutes before sun exposure

● reapply at least every 2 hours

● use a water resistant sunscreen if swimming or sweating

● Sun Protection Measures. Spending time in the sun increases your risk of skin cancer and early skin aging. To decrease this risk, regularly use a sunscreen with a Broad Spectrum SPF value of 15 or higher and other sun protection measures including:

● limit time in the sun, especially from 10 a.m. – 2 p.m.

● wear long-sleeved shirts, pants, hats, and sunglasses

● children under 6 months of age: Ask a doctor

Other information

protect the product in this container from excessive heat and direct sun

Inactive ingredients

dimethicone, C12-15 alkyl benzoate, triethylhexanoin, isohexadecane, talc, hydrogentated jojoba oil, dimethicone crosspolymer, styrene/acrylates copolymer, C30-45 alkyldimethylsilyl polypropylsilsesquioxane, dimethicone/vinyl dimethicone crosspolymer aluminum stearate, alumina, polyhydroxystearic acid, iron oxides, phenoxyethanol, silica silylate, PEG-8 laurate, triethoxycaprylylsilane, 2-oleamido-1,3-octadecanediol, disodium stearoyl glutamate, paraffin, aluminum hydroxide

Questions or comments?

Call 1-800-811-1660

Monday - Friday

(9 a.m. - 5 p.m. CST)